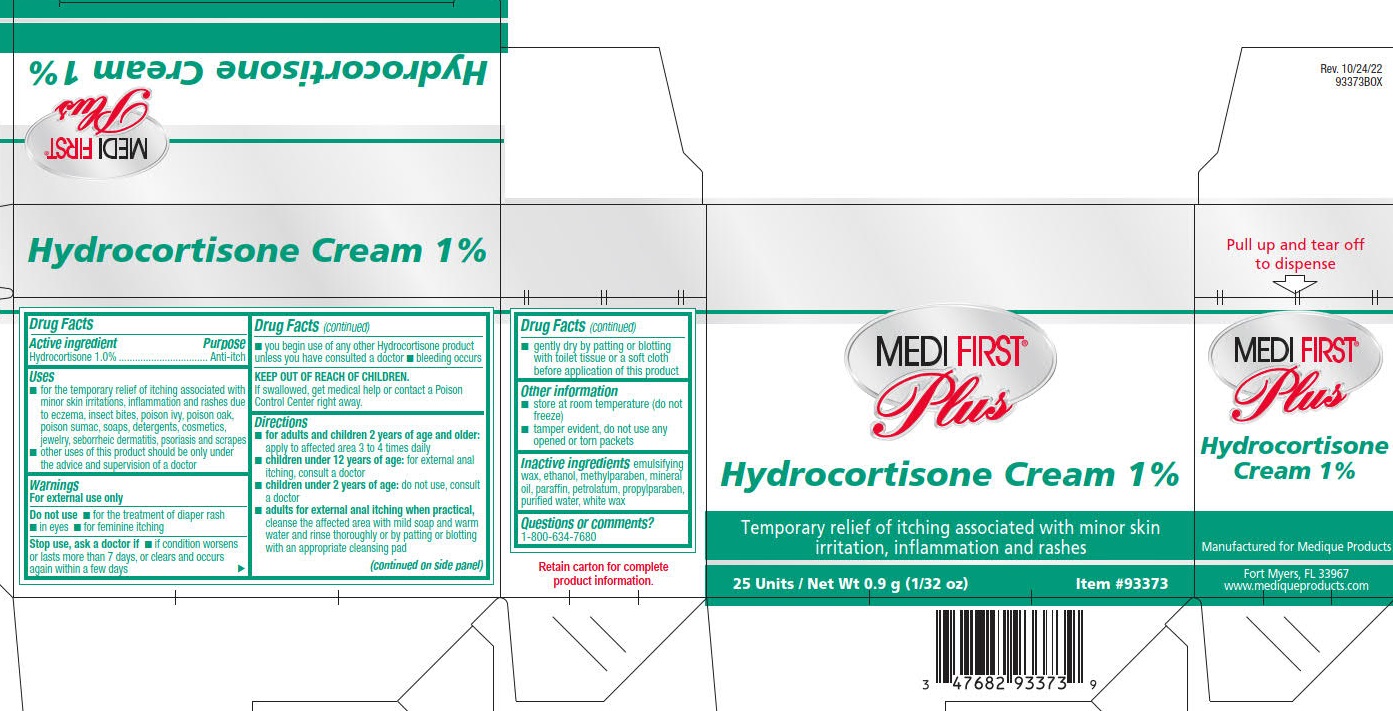 DRUG LABEL: Hydrocortisone
NDC: 47682-933 | Form: CREAM
Manufacturer: Unifirst First Aid Corporation
Category: otc | Type: HUMAN OTC DRUG LABEL
Date: 20250909

ACTIVE INGREDIENTS: HYDROCORTISONE 10 mg/1 g
INACTIVE INGREDIENTS: ALCOHOL; METHYLPARABEN; MINERAL OIL; PARAFFIN; PETROLATUM; PROPYLPARABEN; WATER; WHITE WAX

Medi-First Plus Hydrocortisone Cream

Drug Facts

Active ingredient

Hydrocortisone 1.0%

Purpose

Anti-itch

Uses

- for the temporary relief of itching associated with minor skin irritations, inflammation and rashes
- other uses of this product should be only under the advice and supervision of a doctor

Warnings

For external use only

Do not use

- for the teatment of diaper rash. Consult a doctor

When using this product

- avoid contact with the eyes
- do not begin use of any other hydrocortisone product unless you've consulted a doctor

Stop use and ask a doctor if

- condition worsens
- symptoms persist for more than 7 days
- symptoms clear up and occurs again within a few days

Keep out of reach of children. If swallowed, get medical help or contact a Poison Control Center right away.

Directions

- adults and children 2 years of age and over: apply to affected area not more than 3 to 4 times daily
- children under 2 years of age: do not use, consult a doctor

Other information

- clean the affected area
- store at room temperature (do not freeze)
- tamper evident, do notany opened or torn packets
- you may report a serious adverswe reaction to this product to 800-634-7680

Inactive ingredients

Emulsifying wax, ethanol, methylparaben, mineral oil, paraffin, petrolatum, propylparaben, purified water, white wax

Medi-First Plus Hydrocortisone

MEDI-FIRST®
Plus

Hydrocortisone Cream 1%

Temporary relief of itching associated with monor skin irritations, inflamation and rashes

25 units / Net Wt 0.9 g (1/32 oz)

Item #93373